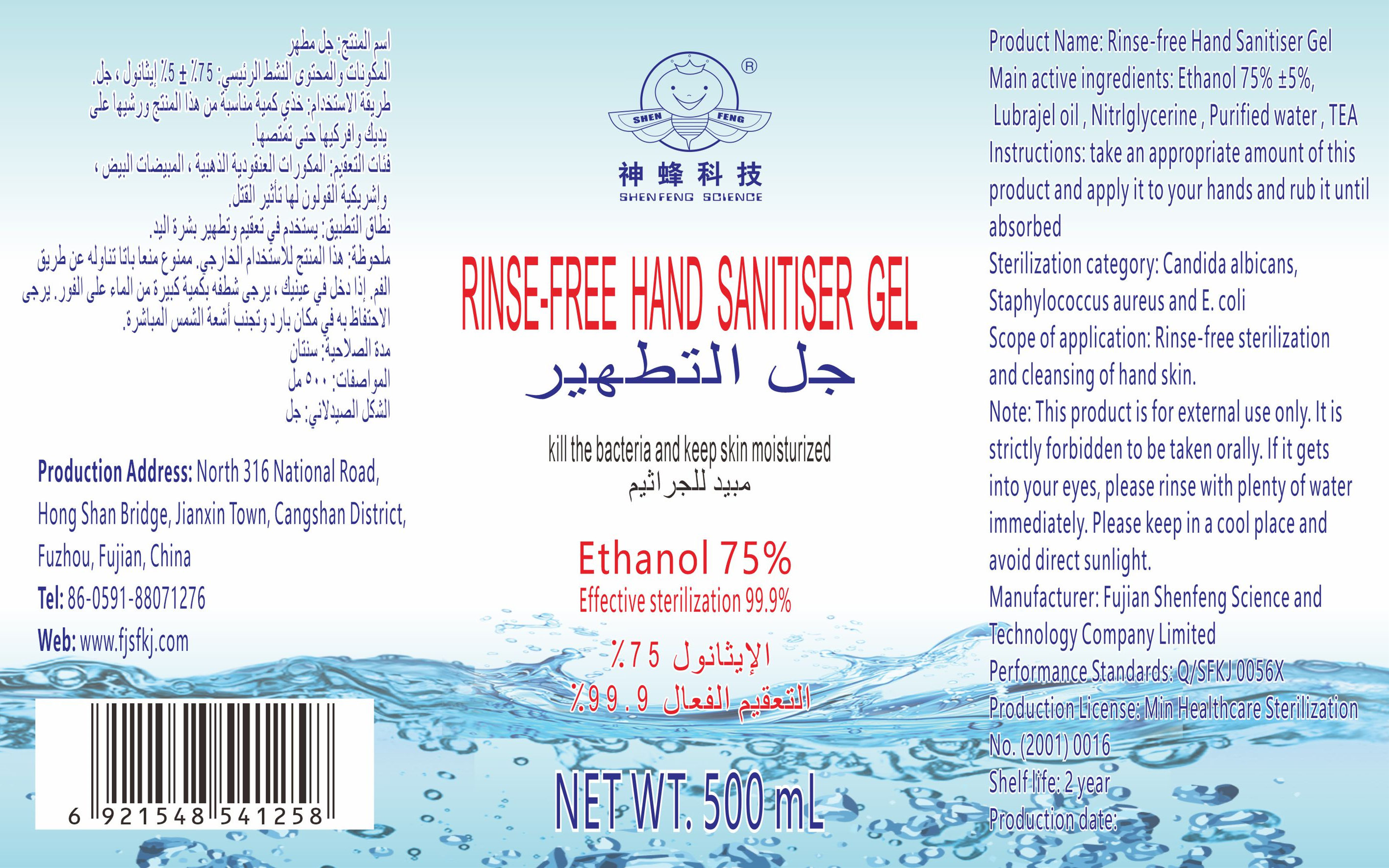 DRUG LABEL: Rinse-free Hand Sanitiser Gel
NDC: 52706-001 | Form: LIQUID
Manufacturer: Fujian Shenfeng Science and Technology Co.,Ltd.
Category: otc | Type: HUMAN OTC DRUG LABEL
Date: 20200423

ACTIVE INGREDIENTS: ALCOHOL 375 mL/500 mL
INACTIVE INGREDIENTS: GLYCERIN; WATER

DOSAGE AND ADMINISTRATION

Please keep in a cool place and avoid direct sunlight

INACTIVE INGREDIENT

water,

glycerol

INDICATIONS AND USAGE

take an appropriate amount of this product and apply ito your hands and rub it until absorbed

ACTIVE INGREDIENT

Alcohol

keep out of children

PURPOSE

Disinfection
Sterilization
No Rinseing

WARNINGS

This productis for externaluse only,Itis strictly fridden to be taken orllyl. lf it gets into your eyes, please rinse with plenty of water
immediately. Please keep in a cool place and avoid direct sunlight